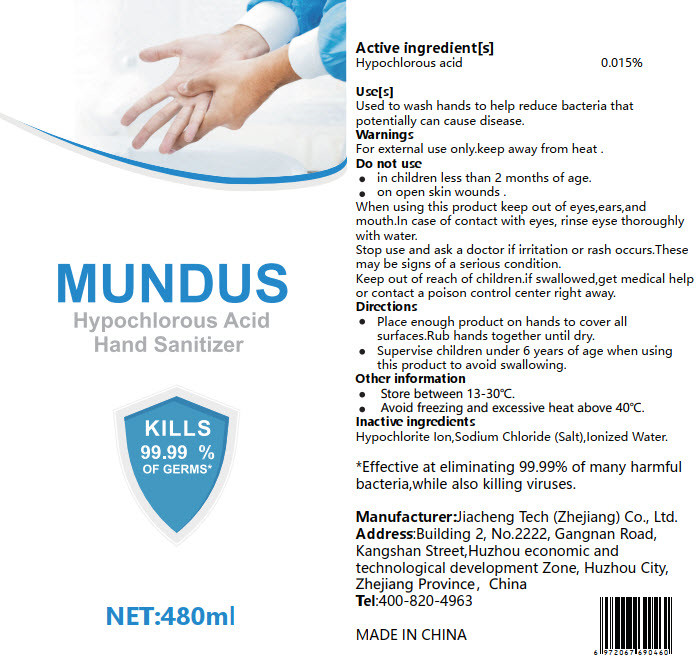 DRUG LABEL: Mundus Hypochlorous Acid Hand Sanitizer
NDC: 55683-001 | Form: GEL
Manufacturer: Jiacheng Tech (Zhejiang) Co., Ltd.
Category: otc | Type: HUMAN OTC DRUG LABEL
Date: 20201015

ACTIVE INGREDIENTS: HYPOCHLOROUS ACID 0.072 g/480 mL
INACTIVE INGREDIENTS: WATER

DOSAGE AND ADMINISTRATION

Keep in dry and cool, avoid direct sunlight and high temperature environment.

INACTIVE INGREDIENT

Purified Water

INDICATIONS AND USAGE

1.Pump a samll amount into palms.
2.Rub thoroughly over all surfaces of both hands.
3.Rub hands together briskly until dry.

ACTIVE INGREDIENT

Hypochlorous acid

Keep out of reach of children.

Stop use and ask a doctor if irritation and/or redness develop.

PURPOSE

Disinfection
Sterilization
No Rinseing

WARNINGS

1.Keep in dry and cool, avoid direct sunlight and high temperature environment.
2.Keep out of reach of children.
3.Stop use and ask a doctor if irritation and/or redness develop.